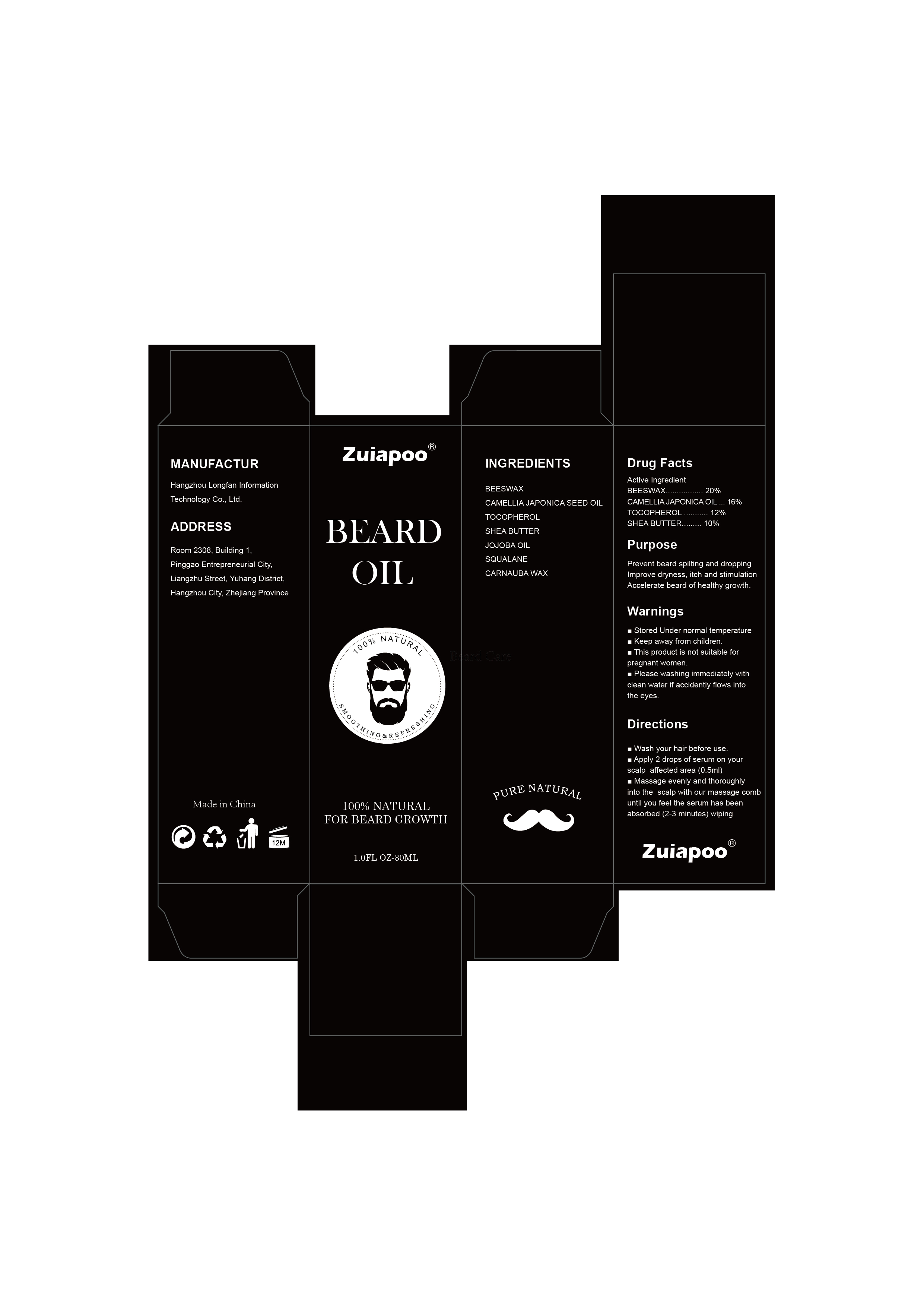 DRUG LABEL: Beard growth oil
NDC: 84650-001 | Form: LIQUID
Manufacturer: Hangzhou Longfan Information Technology Co., Ltd.
Category: otc | Type: HUMAN OTC DRUG LABEL
Date: 20240819

ACTIVE INGREDIENTS: SHEA BUTTER 10 g/100 mL; CAMELLIA JAPONICA SEED OIL 16 g/100 mL; TOCOPHEROL 12 g/100 mL; YELLOW WAX 20 g/100 mL
INACTIVE INGREDIENTS: CARNAUBA WAX; JOJOBA OIL; SQUALANE

Beard growth oil

ACTIVE INGREDIENT

BEESWAX 20%
CAMELLIA JAPONICA SEED OIL 16%
TOCOPHEROL 12%
SHEA BUTTER 10%

PURPOSE

Prevent beard spilting and droppingImprove dryness, itch and stimulationAccelerate beard ofhealthy growth

Keep away from children.

INDICATIONS AND USAGE

Prevent beard spilting and droppingImprove dryness, itch and stimulationAccelerate beard of healthy growth

WARNINGS

Stored Under normal temperature.
Keep away from children.
This product is not suitable for Pregnant women.
Please washing immediately withclean water.
if accidently flows into the eyes.

DOSAGE AND ADMINISTRATION

Wash your hair before use
Apply 2 drops of serum on yourscalp affected area (0.5ml)
Massage evenly and thoroughlyinto the scalp with our massage combuntil you feel the serum has beenabsorbed (2-3 minutes) wiping

STORAGE AND HANDLING

Stored Under normal temperature.

INACTIVE INGREDIENT

JOJOBA OIL
SQUALANE
CARNAUBA WAX